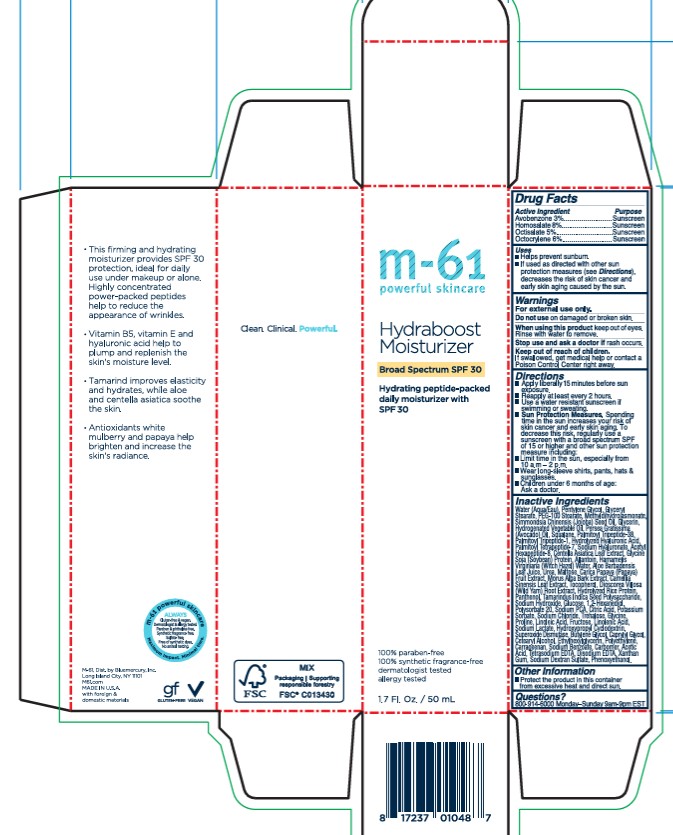 DRUG LABEL: Hydraboost Moisturizer SPF 30
NDC: 72203-001 | Form: LOTION
Manufacturer: Bluemercury
Category: otc | Type: HUMAN OTC DRUG LABEL
Date: 20251209

ACTIVE INGREDIENTS: AVOBENZONE 30 mg/1 mL; HOMOSALATE 80 mg/1 mL; OCTISALATE 50 mg/1 mL; OCTOCRYLENE 60 mg/1 mL
INACTIVE INGREDIENTS: CARICA PAPAYA (PAPAYA) FRUIT JUICE; GLUCOSE; PERSEA GRATISSIMA (AVOCADO) OIL; HYALURONIC ACID; MORUS ALBA BARK; XANTHAN GUM; ETHYLHEXYLGLYCERIN; POTASSIUM SORBATE; ALLANTOIN; POLYETHYLENE; HAMAMELIS VIRGINIANA (WITCH HAZEL) LEAF WATER; HYDROGENATED PALM KERNEL OIL; CITRIC ACID; DEXTRAN SULFATE SODIUM (5000 MW); PANTHENOL; GLYCINE; GLYCINE SOJA (SOYBEAN) STEROLS; TOCOPHEROL; SODIUM PCA; MALTOSE; METHYLDIHYDROJASMONATE; 1,2-HEXANEDIOL; PHENOXYETHANOL; HYDROLYZED RICE PROTEIN (ENZYMATIC; 2000 MW); FRUCTOSE; SUPEROXIDE DISMUTASE; PALMITOYL TRIPEPTIDE-1; CARRAGEENAN; CARBOMER; WATER; DIOSCOREA VILLOSA ROOT; TETRASODIUM EDTA; CETEARYL ALCOHOL; SQUALANE; TREHALOSE; GLYCERYL STEARATE; PENTYLENE GLYCOL; PEG-100 STEARATE; SIMMONDSIA CHINENSIS (JOJOBA) SEED OIL; GLYCERIN; PROLINE; ALOE BARBADENSIS LEAF JUICE; LINOLEIC ACID; HYDROXYPROPYL BETADEX; TAMARINDUS INDICA SEED; CENTELLA ASIATICA LEAF WATER; CAMELLIA SINENSIS LEAF; UREA; LINOLENIC ACID; SODIUM HYALURONATE; SODIUM LACTATE; ACETYL HEXAPEPTIDE-8; PALMITOYL TRIPEPTIDE-38; PALMITOYL TETRAPEPTIDE-7; BUTYLENE GLYCOL; CAPRYLYL GLYCOL; POLYSORBATE 20; EDETATE DISODIUM; SODIUM CHLORIDE; SODIUM BENZOATE; ACETIC ACID; SODIUM HYDROXIDE

Hydraboost Moisturizer SPF 30

Drug Facts

ACTIVE INGREDIENT

Active Ingredients | Purpose
Avobenzone 3% | sunscreen
Homosalate 8% | sunscreen
Octisalate 5% | sunscreen
Octocrylene 6% | sunscreen

Uses

- Helps prevent sunburn.
- If used as directed with other sun protection measures (see Directions), decreases the risk of skin cancer and early skin aging caused by the sun.

Warnings

For external use only.

Do not use on damaged or broken skin.

When using this product keep out of eyes. Rinse with water to remove.

Stop use and ask a doctor if rash occurs.

Keep out of reach of children.

If swallowed, get medical help or contact a Poison Control Center right away.

Directions

- Apply liberally 15 minutes before sun exposure.
- Reapply at least every 2 hours.
- Use a water resistant sunscreen if swimming or sweating.
- Sun Protection Measures. Spending time in the sun increases your risk of skin cancer and early skin aging. To decrease this risk, regularly use a sunscreen with a broad spectrum SPF of 15 or higher and other sun protection measure including:
  - Limit time in the sun, especially from 10am-2pm.
  - Wear long-sleeve shirts, pants, hats & sunglasses.
- Children under 6 months of age:
  Ask a doctor.

Inactive Ingredients

Water (Aqua/Eau), Pentylene Glycol, Glyceryl Stearate, PEG-100 Stearate, Methyldihydrojasmonate, Simmondsia Chinensis (Jojoba) Seed Oil, Glycerin, Hydrogenated Vegetable Oil, Persea Gratissima (Avocado) Oil, Squalane, Hamamelis Virginiana (Witch Hazel) Water, Trehalose, Sodium PCA, Panthenol, Glycine, Proline, Aloe Barbadensis Leaf Juice, Linoleic Acid, Hydrolyzed Rice Protein, Fructose, Urea, Linolenic Acid, Sodium Hyaluronate, Sodium Lactate, Hydrolyzed Hyaluronic Acid, Hydroxypropyl Cyclodextrin, Tamarindus Indica Seed Polysaccharide, Centella Asiatica Leaf Extract, Allantoin, Maltose, Carica Papaya (Papaya) Fruit Extract, Morus Alba Bark Extract, Glycine Soja (Soybean) Protein, Camellia Sinensis Leaf Extract, Tocopherol, Dioscorea Villosa (Wild Yam) Root Extract, Acetyl Hexapeptide-8, Sodium Dextran Sulfate, Superoxide Dismutase, Glucose, Palmitoyl Tripeptide-38, Palmitoyl Tripeptide-1, Palmitoyl Tetrapeptide-7, Butylene Glycol, Caprylyl Glycol, Cetearyl Alcohol, Carrageenan, Carbomer, Xanthan Gum, Polysorbate 20, Ethylhexylglycerin, Potassium Sorbate, Tetrasodium EDTA, Disodium EDTA, Citric Acid, Sodium Hydroxide, Polyethylene, Sodium Chloride, 1,2-Hexanediol, Sodium Benzoate, Acetic Acid, Phenoxyethanol.

Other Information

- Protect the product in this container from excessive heat and direct sun.

Questions?

800-914-6000 9-5pm EST, Monday- Friday

PRINCIPAL DISPLAY PANEL - 50 mL Bottle Carton

m-61®
powerful skincare

Hydraboost
Moisturizer
SPF 30

HYDRATING PEPTIDE
AND VITAMIN B5
MOISTURIZER

BROAD SPECTRUM
SPF30 SUNSCREEN

Peptide-packed vitamin B5
hydrating and firming
daily moisturizer with
SPF30, tamarind & aloe

all skin types

100% paraben-free
100% synthetic fragrance-free
dermatologist tested
allergy tested

50 mL e 1.7 FL. OZ.